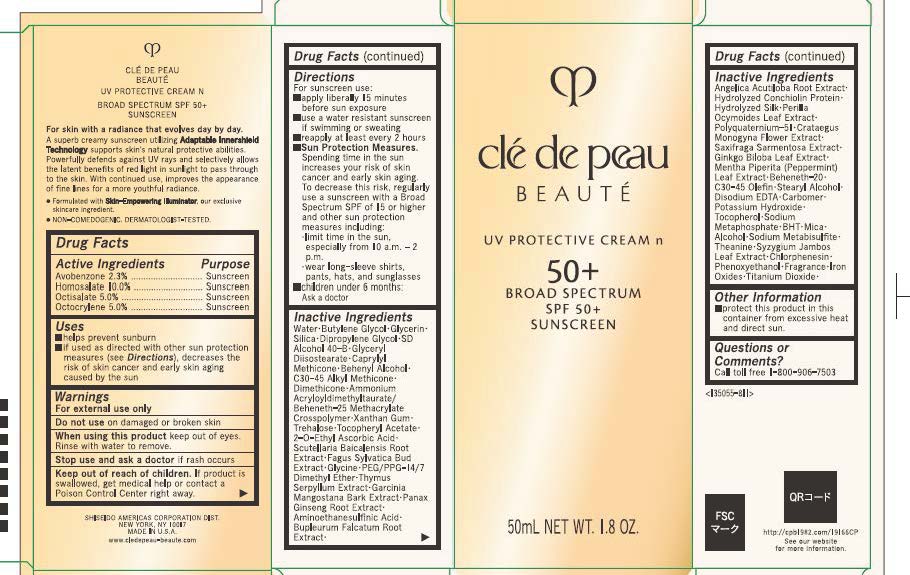 DRUG LABEL: cle de peau BEAUTE UV PROTECTIVE N
NDC: 58411-968 | Form: CREAM
Manufacturer: Shiseido Americas Corporation
Category: otc | Type: HUMAN OTC DRUG LABEL
Date: 20260204

ACTIVE INGREDIENTS: AVOBENZONE 1.19715 g/50 mL; HOMOSALATE 5.205 g/50 mL; OCTISALATE 2.6025 g/50 mL; OCTOCRYLENE 2.6025 g/50 mL
INACTIVE INGREDIENTS: WATER; BUTYLENE GLYCOL; GLYCERIN; SILICA; DIPROPYLENE GLYCOL; GLYCERYL DIISOSTEARATE; CAPRYLYL METHICONE; BEHENYL ALCOHOL; C30-45 ALKYL METHICONE; DIMETHICONE; AMMONIUM ACRYLOYLDIMETHYLTAURATE/BEHENETH-25 METHACRYLATE CROSSPOLYMER (52000 MPA.S); XANTHAN GUM; TREHALOSE; .ALPHA.-TOCOPHEROL ACETATE; 2-O-ETHYL ASCORBIC ACID; SCUTELLARIA BAICALENSIS ROOT; FAGUS SYLVATICA FLOWER BUD; GLYCINE; PEG/PPG-14/7 DIMETHYL ETHER; THYMUS SERPYLLUM WHOLE; GARCINIA MANGOSTANA BARK; ASIAN GINSENG; AMINOETHANESULFINIC ACID; BUPLEURUM FALCATUM ROOT; ANGELICA ACUTILOBA ROOT; POLYQUATERNIUM-51 (2-METHACRYLOYLOXYETHYL PHOSPHORYLCHOLINE/N-BUTYL METHACRYLATE; 3:7); PERILLA FRUTESCENS LEAF; CRATAEGUS MONOGYNA FLOWER; SAXIFRAGA STOLONIFERA LEAF; GINKGO; MENTHA PIPERITA LEAF; STEARYL ALCOHOL; EDETATE DISODIUM; CARBOMER; POTASSIUM HYDROXIDE; TOCOPHEROL; SODIUM METAPHOSPHATE; BHT; MICA; ALCOHOL; SODIUM METABISULFITE; THEANINE; SYZYGIUM JAMBOS LEAF; CHLORPHENESIN; PHENOXYETHANOL; TITANIUM DIOXIDE; FERRIC OXIDE RED

cle de peau BEAUTE UV PROTECTIVE N

Drug Facts

Active Ingredients | Purpose
Avobenzone 2.3% | Sunscreen
Homsalate 10% | Sunscreen
Octisalate 5% | Sunscreen
Octocrylene 5% | Sunscreen

Uses

- helps prevent sunburn
- if used as directed with other sun protection measures (see Directions), decreases the risk of skin cancer and early skin aging caused by the sun

Warnings

For external use only

Do not useon damaged or broken skin

WHEN USING

When using this productkeep out of eyes. Rinse with water to remove.

Stop use and ask a doctorif rash occurs

Keep out of reach of children.If product is swallowed, get medical help or contact a Poison Control Center right away.

Directions

For sunscreen use:

- apply liberally 15 minutes before sun exposure
- use a water resistant sunscreen if swimming or sweating
- reapply at least every 2 hours
- Sun Protection Measures. Spending time in the sun increases your risk of skin cancer and early skin aging. To decrease this risk, regularly use a sunscreen with a broad spectrum SPF of 15 or higher and other sun protection measures including:
- limit time in the sun, especially from 10 a.m. - 2p.m.
- wear long-sleeve shirts, pant, hats, and sunglasses
- children under 6 months: Ask a doctor

INACTIVE INGREDIENT

WATER･BUTYLENE GLYCOL･GLYCERIN･SILICA･DIPROPYLENE GLYCOL･SD ALCOHOL 40-B･GLYCERYL DIISOSTEARATE･CAPRYLYL METHICONE･BEHENYL ALCOHOL･C30-45 ALKYL METHICONE･DIMETHICONE･AMMONIUM ACRYLOYLDIMETHYLTAURATE/BEHENETH-25 METHACRYLATE CROSSPOLYMER･XANTHAN GUM･TREHALOSE･TOCOPHERYL ACETATE･2-O-ETHYL ASCORBIC ACID･SCUTELLARIA BAICALENSIS ROOT EXTRACT･FAGUS SYLVATICA BUD EXTRACT･GLYCINE･PEG/PPG-14/7 DIMETHYL ETHER･THYMUS SERPYLLUM EXTRACT･GARCINIA MANGOSTANA BARK EXTRACT･PANAX GINSENG ROOT EXTRACT･AMINOETHANESULFINIC ACID･BUPLEURUM FALCATUM ROOT EXTRACT･ANGELICA ACUTILOBA ROOT EXTRACT･HYDROLYZED CONCHIOLIN PROTEIN･HYDROLYZED SILK･PERILLA OCYMOIDES LEAF EXTRACT･POLYQUATERNIUM-51･CRATAEGUS MONOGYNA FLOWER EXTRACT･SAXIFRAGA SARMENTOSA EXTRACT･GINKGO BILOBA LEAF EXTRACT･MENTHA PIPERITA (PEPPERMINT) LEAF EXTRACT･BEHENETH-20･C30-45 OLEFIN･STEARYL ALCOHOL･DISODIUM EDTA･CARBOMER･POTASSIUM HYDROXIDE･TOCOPHEROL･SODIUM METAPHOSPHATE･BHT･MICA･ALCOHOL･SODIUM METABISULFITE･THEANINE･SYZYGIUM JAMBOS LEAF EXTRACT･CHLORPHENESIN･PHENOXYETHANOL･FRAGRANCE･IRON OXIDES･TITANIUM DIOXIDE･

Other Information

- protect this product in this container from excessive heat and direct sun.

Questions or Comments?

Call toll free 1-800-906-7503

PRINCIPLE DISPLAY PANNEL 50 mL TUBE

cle de peau

BEAUTE

UV PROTECTIVE CREAM n

50+

BROAD SPECTRUM

SPF 50+

SUNSCREEN

50mL NET WT. 1.8 OZ.